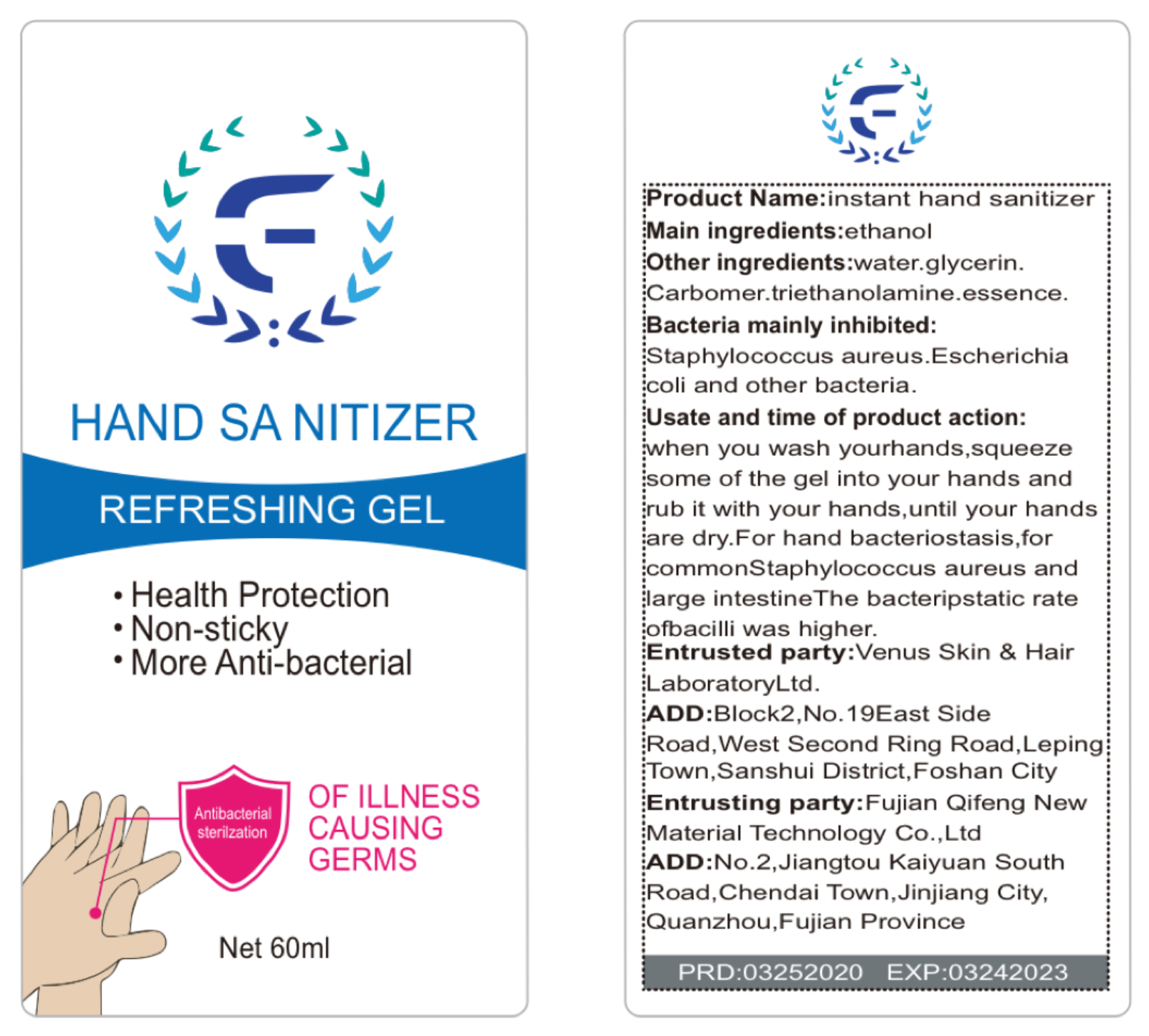 DRUG LABEL: Qifeng Brand Disposable Hand Wash
NDC: 75113-001 | Form: GEL
Manufacturer: Fujian Qifeng New Material Technology Co., Ltd
Category: otc | Type: HUMAN OTC DRUG LABEL
Date: 20200410

ACTIVE INGREDIENTS: ALCOHOL 68 mL/100 mL
INACTIVE INGREDIENTS: TROLAMINE; GLYCERIN; CARBOMER INTERPOLYMER TYPE A (ALLYL SUCROSE CROSSLINKED); WATER

Qifeng Brand Disposable Hand Wash Gel

Active Ingredient(s)

Alcohol 68% v/v. Purpose: Antiseptic

Purpose

Antiseptic, Hand Sanitizer

Use

Antibacterial sterilization

Warnings

For external use only. Flammable. Keep away from heat or flame

Do not use

on open skin wounds

When using this product keep out of eyes, ears, and mouth. In case of contact with eyes, rinse eyes thoroughly with water.
Stop use and ask a doctor if irritation or rash occurs. These may be signs of a serious condition.
Keep out of reach of children. If swallowed, get medical help or contact a Poison Control Center right away.

Stop use and ask a doctor if irritation or rash occurs. These may be signs of a serious condition.

Keep out of reach of children. If swallowed, get medical help or contact a Poison Control Center right away.

Directions

When you wash your hands, squeeze some of the gel into your hands and rub it with your hands, until your hands are dry.

Other information

Bacteria mainly inhibited: Staphylococcus aureus. Escherichia coli and other bacteria

Inactive ingredients

water, glycerin, carbomer, triethanolamine, essence

Package Label - Principal Display Panel

60ml 75113-001-01